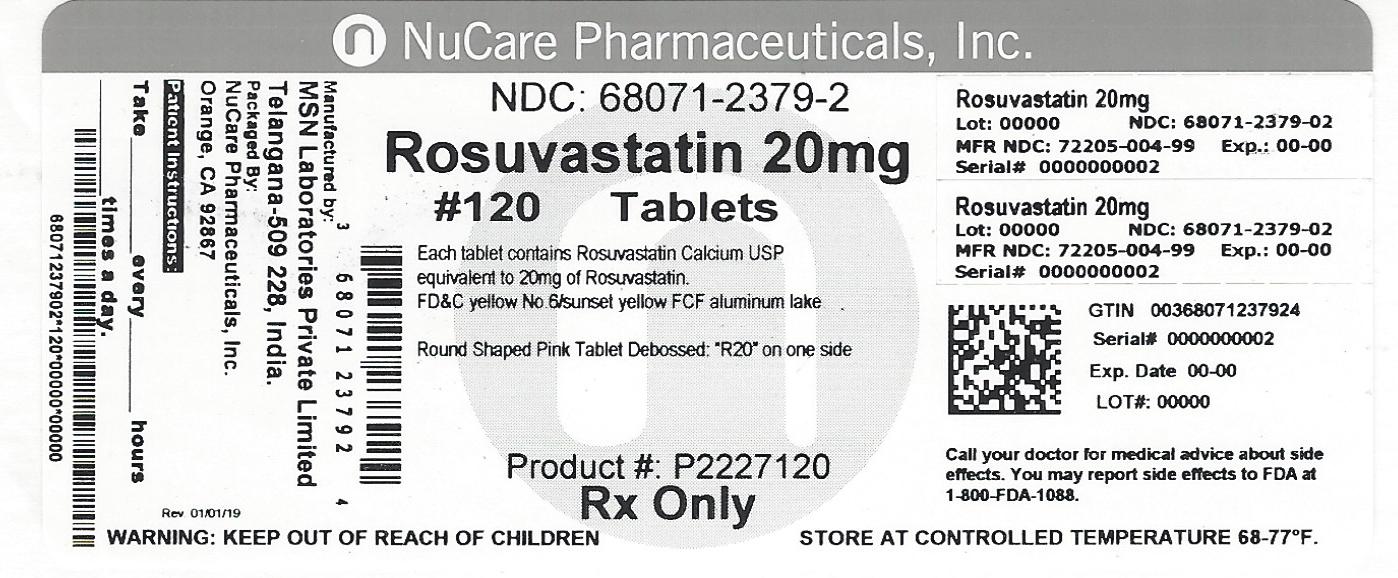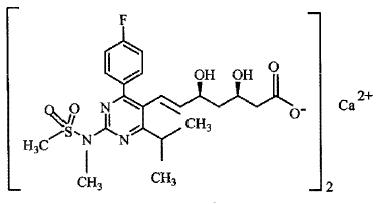 DRUG LABEL: Rosuvastatin Calcium
NDC: 68071-2379 | Form: TABLET, FILM COATED
Manufacturer: NuCare Pharmaceuticals,Inc.
Category: prescription | Type: HUMAN PRESCRIPTION DRUG LABEL
Date: 20260302

ACTIVE INGREDIENTS: ROSUVASTATIN CALCIUM 20 mg/1 1
INACTIVE INGREDIENTS: CROSPOVIDONE; MAGNESIUM STEARATE; MANNITOL; MEGLUMINE; CELLULOSE, MICROCRYSTALLINE; HYPROMELLOSES; TITANIUM DIOXIDE; TRIACETIN; FD&C RED NO. 40; FD&C YELLOW NO. 6; FD&C BLUE NO. 2; STARCH, CORN; LACTOSE MONOHYDRATE

HIGHLIGHTS OF PRESCRIBING INFORMATION

These highlights do not include all the information needed to use ROSUVASTATIN TABLETS safely and effectively. See full prescribing information for ROSUVASTATIN TABLETS.
ROSUVASTATIN tablets, for oral use
Initial U.S. Approval: 2003

1 INDICATIONS AND USAGE

Rosuvastatin tablets are an HMG Co-A reductase inhibitor indicated for:

- adult patients with hypertriglyceridemia as an adjunct to diet (1.3)
- adult patients with primary dysbetalipoproteinemia (Type III hyperlipoproteinemia) as an adjunct to diet (1.4)
- adult patients with homozygous familial hypercholesterolemia (HoFH) to reduce LDL-C, total-C, and ApoB (1.5)

Limitations of use (1.8): Rosuvastatin tablets has not been studied in Fredrickson Type I and V dyslipidemias.

2 DOSAGE AND ADMINISTRATION

- Rosuvastatin tablets can be taken with or without food, at any time of day. (2.1)
- Dose range: 5 to 40 mg once daily. Use 40 mg dose only for patients not reaching LDL-C goal with 20 mg. (2.1)
- Adult HoFH :Starting dose 20 mg/day. (2.1)

3 DOSAGE FORMS AND STRENGTHS

Tablets: 5 mg, 10 mg, 20 mg, and 40 mg (3)

4 CONTRAINDICATIONS

- Known hypersensitivity to product components (4)
- Active liver disease, which may include unexplained persistent elevations in hepatic transaminase levels (4)
- Preganancy (4, 8.1, 8.3)
- Lactation (4, 8.2)

5 WARNINGS AND PRECAUTIONS

- Skeletal muscle effects (e.g., myopathy and rhabdomyolysis): Risks increase with use of 40 mg dose, advanced age (≥65), hypothyroidism, renal impairment, and combination use with cyclosporine, atazanavir/ritonavir, lopinavir/ ritonavir, or simeprevir. Cases of myopathy and rhabdomyolysis with acute renal failure secondary to myoglobinuria have been reported. Advise patients to promptly report to their physician unexplained and/or persistent muscle pain, tenderness, or weakness and discontinue rosuvastatin calcium tablets if signs or symptoms appear. (5.1, 7.5, 7.6)
- Liver enzyme abnormalities: Persistent elevations in hepatic transaminases can occur. Perform liver enzyme tests before initiating therapy and as clinically indicated thereafter. (5.2)

6 ADVERSE REACTIONS

Most frequent adverse reactions (rate ≥2%) are headache, myalgia, abdominal pain, asthenia, and nausea. (6.1)
To report SUSPECTED ADVERSE REACTIONS, contact Novadoz Pharmaceuticals LLc. at 1-855-668-2369 or FDA at 1-800-FDA-1088 or www.fda.gov/medwatch.

7 DRUG INTERACTIONS

- Cyclosporine: Combination increases rosuvastatin exposure. Limit rosuvastatin calcium dose to 5 mg once daily. (2.4, 5.1, 7.1, 12.3)
- Gemfibrozil: Combination should be avoided. If used together, limit rosuvastatin calcium dose to 10 mg once daily.(2.4, 5.1, 7.2)
- Atazanavir/ritonavir, lopinavir/ritonavir, or simeprevir: Combination increases rosuvastatin exposure. Limit rosuvastatin calcium dose to 10 mg once daily. (2.4, 5.1, 7.3, 12.3)
- Coumarin anticoagulants: Combination prolongs INR. Achieve stable INR prior to starting rosuvastatin calcium. Monitor INR frequently until stable upon initiation or alteration of rosuvastatin calcium therapy. (5.3, 7.4)
- Concomitant lipid-lowering therapies: Use with fibrates or lipid- modifying doses (≥1 g/day) of niacin increases the risk of adverse skeletal muscle effects. Caution should be used when prescribing with rosuvastatin calcium. (5.1, 7.5, 7.6)

8 USE IN SPECIFIC POPULATIONS

- Females of reproductive potential: Advise females of reproductive potential to use effective contraception during treatment with rosuvastatin calcium (8.3)
- Severe renal impairment (not on hemodialysis): Starting dose is 5 mg, not to exceed 10 mg. (2.5, 5.1, 8.6)
- Asian population: Consider 5 mg starting dose. (2.3, 8.8)

Pediatric use information for patients 7 to 17 years of age is approved for AstraZeneca’s CRESTOR (rosuvastatin calcium) tablets. However, due to AstraZeneca’s marketing exclusivity rights, this drug product is not labeled with that pediatric information.

FULL PRESCRIBING INFORMATION

1 INDICATIONS AND USAGE

Pediatric use information for patients 7 to 17 years of age is approved for AstraZeneca’s CRESTOR (rosuvastatin calcium) tablets. However, due to AstraZeneca’s marketing exclusivity rights, this drug product is not labeled with that pediatric information.

1.3 Hypertriglyceridemia

Rosuvastatin tablets are indicated as adjunctive therapy to diet for the treatment of adult patients with hypertriglyceridemia.

1.4 Primary Dysbetalipoproteinemia (Type III Hyperlipoproteinemia)

Rosuvastatin tablets are indicated as an adjunct to diet for the treatment of adult patients with primary dysbetalipoproteinemia (Type III Hyperlipoproteinemia).

1.5 Adult Patients with Homozygous Familial Hypercholesterolemia

Rosuvastatin tablets are indicated as adjunctive therapy to other lipid-lowering treatments (e.g., LDL apheresis) or alone if such treatments are unavailable to reduce LDL-C, Total-C, and ApoB in adult patients with homozygous familial hypercholesterolemia.

1.8 Limitations of Use

Rosuvastatin tablets have not been studied in Fredrickson Type I and V dyslipidemias.

2 DOSAGE AND ADMINISTRATION

2.1 General Dosing Information

The dose range for rosuvastatin tablets in adults is 5 to 40 mg orally once daily. The usual starting dose is 10 to 20 mg once daily. The usual starting dose in adult patients with homozygous familial hypercholesterolemia is 20 mg once daily.
The maximum rosuvastatin calcium tablets dose of 40 mg should be used only for those patients who have not achieved their LDL-C goal utilizing the 20 mg dose [see Warnings and Precautions (5.1)].

Rosuvastatin tablets can be administered as a single dose at any time of day, with or without food. The tablet should be swallowed whole.

When initiating rosuvastatin tablets therapy or switching from another HMG-CoA reductase inhibitor therapy, the appropriate rosuvastatin calcium tablets starting dose should first be utilized, and only then titrated according to the patient’s response and individualized goal of therapy.

After initiation or upon titration of rosuvastatin tablets, lipid levels should be analyzed within 2 to 4 weeks and the dosage adjusted accordingly.

Pediatric use information for patients 7 to 17 years of age is approved for AstraZeneca’s CRESTOR (rosuvastatin calcium) tablets. However, due to AstraZeneca’s marketing exclusivity rights, this drug product is not labeled with that pediatric information.

2.3 Dosing in Asian Patients

In Asian patients, consider initiation of rosuvastatin tablets therapy with 5 mg once daily due to increased rosuvastatin plasma concentrations. The increased systemic exposure should be taken into consideration when treating Asian patients not adequately controlled at doses up to 20 mg/day. [see Use in Specific Populations (8.8) and ClinicalPharmacology (12.3)].

2.4 Use with Concomitant Therapy

Patients taking cyclosporine

The dose of rosuvastatin tablets should not exceed 5 mg once daily [see Warnings and Precautions (5.1), Drug Interactions (7.1) ,and Clinical Pharmacology (12.3)].

Patients taking gemfibrozil

Avoid concomitant use of rosuvastatin tablets with gemfibrozil. If concomitant use cannot be avoided, initiate rosuvastatin calcium tablets at 5 mg once daily. The dose of rosuvastatin tablets should not exceed 10 mg once daily [see Warnings and Precautions (5.1), Drug Interactions (7.2) and Clinical Pharmacology(12.3)].

Patients taking atazanavir and ritonavir, lopinavir and ritonavir, or simeprevir

Initiate rosuvastatin tablets therapy with 5 mg once daily. The dose of rosuvastatin tablets should not exceed 10 mg once daily [ see Warnings and Precautions (5.1) , Drug Interactions (7.3) ,and Clinical Pharmacology (12.3) ].

2.5 Dosing in Patients with Severe Renal Impairment

For patients with severe renal impairment (CLcr < 30 mL/min/1.73 m^2) not on hemodialysis, dosing of rosuvastatin tablets should be started at 5 mg once daily and not exceed 10 mg once daily [see Use in Specific Populations (8.6) and Clinical Pharmacology (12.3)].

3 DOSAGE FORMS AND STRENGTHS

5 mg: White, round shaped, biconvex, film coated tablets debossed with "R5" on one side and plain on other side.

10 mg: Pink, round shaped, biconvex, film coated tablets debossed with "R10" on one side and plain on other side.

20 mg: Pink, round shaped, biconvex, film coated tablets debossed with "R20" on one side and plain on other side.

40 mg: Pink, oval shaped, biconvex, film coated tablets debossed with "R" on one side and "40" on other side.

4 CONTRAINDICATIONS

Rosuvastatin calcium is contraindicated in the following conditions:

- Patients with a known hypersensitivity to any component of this product. Hypersensitivity reactions including rash, pruritus, urticaria, and angioedema have been reported with rosuvastatin calcium [see Adverse Reactions (6.1)].
- Patients with active liver disease, which may include unexplained persistent elevations of hepatic transaminase levels [see Warnings and Precautions (5.2)].
- Pregnancy [see Use in Specific Populations (8.1, 8.3)] .
- Lactation. Limited data indicate that rosuvastatin calcium is present in human milk. Because statins have the potential for serious adverse reactions in nursing infants, women who require rosuvastatin calcium treatment should not breastfeed their infants [see Use in Specific Populations (8.2)] .

5 WARNINGS AND PRECAUTIONS

5.1 Skeletal Muscle Effects

Cases of myopathy and rhabdomyolysis with acute renal failure secondary to myoglobinuria have been reported with HMG-CoA reductase inhibitors, including rosuvastatin tablets. These risks can occur at any dose level, but are increased at the highest dose (40 mg).

Rosuvastatin calcium should be prescribed with caution in patients with predisposing factors for myopathy (e.g., age ≥ 65 years, inadequately treated hypothyroidism, renal impairment).

The risk of myopathy during treatment with rosuvastatin calcium may be increased with concurrent administration of some other lipid-lowering therapies (fibrates or niacin), gemfibrozil, cyclosporine, atazanavir/ritonavir, lopinavir/ritonavir, or simeprevir [see Dosage and Administration (2) and Drug Interactions (7)]. Cases of myopathy, including rhabdomyolysis, have been reported with HMG-CoA reductase inhibitors, including rosuvastatin, coadministered with colchicine, and caution should be exercised when prescribing rosuvastatin calcium with colchicine [see Drug Interactions (7.7)].

Rosuvastatin calcium therapy should be discontinued if markedly elevated creatine kinase levels occur or myopathy is diagnosed or suspected. Rosuvastatin calcium therapy should also be temporarily withheld in any patient with an acute, serious condition suggestive of myopathy or predisposing to the development of renal failure secondary to rhabdomyolysis (e.g., sepsis, hypotension, dehydration, major surgery, trauma, severe metabolic, endocrine, and electrolyte disorders, or uncontrolled seizures).

There have been rare reports of immune-mediated necrotizing myopathy (IMNM), an autoimmune myopathy, associated with statin use. IMNM is characterized by: proximal muscle weakness and elevated serum creatine kinase, which persist despite discontinuation of statin treatment; muscle biopsy showing necrotizing myopathy without significant inflammation; improvement with immunosuppressive agents.

All patients should be advised to promptly report to their physician unexplained muscle pain, tenderness, or weakness, particularly if accompanied by malaise or fever or if muscle signs and symptoms persist after discontinuing rosuvastatin calcium.

5.2 Liver Enzyme Abnormalities

It is recommended that liver enzyme tests be performed before the initiation of rosuvastatin calcium, and if signs or symptoms of liver injury occur.

Increases in serum transaminases [AST (SGOT) or ALT (SGPT)] have been reported with HMG-CoA reductase inhibitors, including rosuvastatin calcium. In most cases, the elevations were transient and resolved or improved on continued therapy or after a brief interruption in therapy. There were two cases of jaundice, for which a relationship to rosuvastatin calcium therapy could not be determined, which resolved after discontinuation of therapy. There were no cases of liver failure or irreversible liver disease in these trials.

In a pooled analysis of placebo-controlled trials, increases in serum transaminases to > 3 times the upper limit of normal occurred in 1.1% of patients taking rosuvastatin calcium versus 0.5% of patients treated with placebo.

There have been rare postmarketing reports of fatal and non-fatal hepatic failure in patients taking statins, including rosuvastatin. If serious liver injury with clinical symptoms and/or hyperbilirubinemia or jaundice occurs during treatment with rosuvastatin calcium, promptly interrupt therapy. If an alternate etiology is not found, do not restart rosuvastatin calcium.

Rosuvastatin calcium should be used with caution in patients who consume substantial quantities of alcohol and/or have a history of chronic liver disease [see Clinical Pharmacology (12.3)]. Active liver disease, which may include unexplained persistent transaminase elevations, is a contraindication to the use of rosuvastatin calcium [seeContraindications (4)].

5.3 Concomitant Coumarin Anticoagulants

Caution should be exercised when anticoagulants are given in conjunction with rosuvastatin calcium because of its potentiation of the effect of coumarin-type anticoagulants in prolonging the prothrombin time/INR. In patients taking coumarin anticoagulants and rosuvastatin calcium concomitantly, INR should be determined before starting rosuvastatin calcium and frequently enough during early therapy to ensure that no significant alteration of INR occurs [see Drug Interactions (7.4)]

5.4 Proteinuria and Hematuria

In the rosuvastatin clinical trial program, dipstick-positive proteinuria and microscopic hematuria were observed among rosuvastatin calcium treated patients. These findings were more frequent in patients taking rosuvastatin calcium 40 mg, when compared to lower doses of rosuvastatin calcium or comparator HMG-CoA reductase inhibitors, though it was generally transient and was not associated with worsening renal function. Although the clinical significance of this finding is unknown, a dose reduction should be considered for patients on rosuvastatin calcium therapy with unexplained persistent proteinuria and/or hematuria during routine urinalysis testing.

5.5 Endocrine Effects

Increases in HbA1c and fasting serum glucose levels have been reported with HMG-CoA reductase inhibitors, including rosuvastatin calcium. Based on clinical trial data with rosuvastatin calcium, in some instances these increases may exceed the threshold for the diagnosis of diabetes mellitus [see Adverse Reactions (6.1)].
Although clinical studies have shown that rosuvastatin calcium alone does not reduce basal plasma cortisol concentration or impair adrenal reserve, caution should be exercised if rosuvastatin calcium is administered concomitantly with drugs that may decrease the levels or activity of endogenous steroid hormones such as ketoconazole, spironolactone, and cimetidine.

6 ADVERSE REACTIONS

The following serious adverse reactions are discussed in greater detail in other sections of the label:

- Rhabdomyolysis with myoglobinuria and acute renal failure and myopathy (including myositis) [see Warnings and Precautions (5.1)]
- Liver enzyme abnormalities [see Warnings and Precautions (5.2)]

6.1 Clinical Studies Experience

Because clinical studies are conducted under widely varying conditions, adverse reaction rates observed in the clinical studies of a drug cannot be directly compared to rates in the clinical studies of another drug and may not reflect the rates observed in clinical practice.
In the rosuvastatin calcium controlled clinical trials database (placebo or active-controlled) of 5394 patients with a mean treatment duration of 15 weeks, 1.4% of patients discontinued due to adverse reactions. The most common adverse reactions that led to treatment discontinuation were:

- myalgia
- abdominal pain
- nausea

The most commonly reported adverse reactions (incidence ≥ 2%) in the rosuvastatin calcium controlled clinical trial database of 5394 patients were:

- headache
- myalgia
- abdominal pain
- asthenia
- nausea

Adverse reactions reported in ≥ 2% of patients in placebo-controlled clinical studies and at a rate greater than placebo are shown in Table 1. These studies had a treatment duration of up to 12 weeks.

Table 1. Adverse Reactions^1 Reported in ≥2% of Patients Treated with rosuvastatin calcium and > Placebo in Placebo-Controlled Trials (% of Patients)

Adverse Reactions | Rosuvastatin calcium 5 mg N=291 | Rosuvastatin calcium 10 mg N=283 | Rosuvastatin calcium 20 mg N=64 | Rosuvastatin calcium 40 mg N=106 | Total Rosuvastatin calcium 5 mg to 40 mg N=744 | Placebo N=382
Headache | 5.5 | 4.9 | 3.1 | 8.5 | 5.5 | 5
Nausea | 3.8 | 3.5 | 6.3 | 0 | 3.4 | 3.1
Myalgia | 3.1 | 2.1 | 6.3 | 1.9 | 2.8 | 1.3
Asthenia | 2.4 | 3.2 | 4.7 | 0.9 | 2.7 | 2.6
Constipation | 2.1 | 2.1 | 4.7 | 2.8 | 2.4 | 2.4

^1Adverse reactions by COSTART preferred term
Other adverse reactions reported in clinical studies were abdominal pain, dizziness, hypersensitivity (including rash, pruritus, urticaria, and angioedema) and pancreatitis. The following laboratory abnormalities have also been reported: dipstick-positive proteinuria and microscopic hematuria [see Warnings and Precautions (5.4)]; elevated creatine phosphokinase, transaminases, glucose, glutamyl transpeptidase, alkaline phosphatase, and bilirubin; and thyroid function abnormalities.
In a clinical trial, involving 981 participants treated with rosuvastatin 40 mg (n=700) or placebo (n=281) with a mean treatment duration of 1.7 years, 5.6% of subjects treated with rosuvastatin calcium versus 2.8% of placebo-treated subjects discontinued due to adverse reactions. The most common adverse reactions that led to treatment discontinuation were: myalgia, hepatic enzyme increased, headache, and nausea.
Adverse reactions reported in ≥ 2% of patients and at a rate greater than placebo are shown in Table 2.

Table 2. Adverse Reactions ^1 Reported in ≥ 2% of Patients Treated with Rosuvastatin calcium and > Placebo in a Trial (% of Patients)

Adverse Reactions | Rosuvastatin calcium 40 mg N=700 | Placebo N=281
Myalgia | 12.7 | 12.1
Arthralgia | 10.1 | 7.1
Headache | 6.4 | 5.3
Dizziness | 4.0 | 2.8
Increased CPK | 2.6 | 0.7
Abdominal pain | 2.4 | 1.8
ALT > 3x ULN ^2 | 2.2 | 0.7

^1Adverse reactions by MedDRA preferred term.

^2Frequency recorded as abnormal laboratory value.
In a clinical trial, 17,802 participants were treated with rosuvastatin 20 mg (n=8901) or placebo (n=8901) for a mean duration of 2 years. A higher percentage of rosuvastatin-treated patients versus placebo-treated patients, 6.6% and 6.2%, respectively, discontinued study medication due to an adverse event, irrespective of treatment causality. Myalgia was the most common adverse reaction that led to treatment discontinuation.
There was a significantly higher frequency of diabetes mellitus reported in patients taking rosuvastatin (2.8%) versus patients taking placebo (2.3%). Mean HbA1c was significantly increased by 0.1% in rosuvastatin-treated patients compared to placebo-treated patients. The number of patients with a HbA1c > 6.5% at the end of the trial was significantly higher in rosuvastatin-treated versus placebo-treated patients [see Warnings and Precautions (5.5)].
Adverse reactions reported in ≥ 2% of patients and at a rate greater than placebo are shown in Table 3.

Table 3. Adverse Reactions ^1Reported in ≥ 2% of Patients Treated with Rosuvastatin calcium and > Placebo in a Trial (% of Patients)

Adverse Reactions | Rosuvastatin calcium 20 mg N=8901 | Placebo N=8901
Myalgia | 7.6 | 6.6
Arthralgia | 3.8 | 3.2
Constipation | 3.3 | 3.0
Diabetes mellitus | 2.8 | 2.3
Nausea | 2.4 | 2.3

^1Treatment-emergent adverse reactions by MedDRA preferred term.

6.2 Postmarketing Experience

The following adverse reactions have been identified during postapproval use of rosuvastatin calcium: arthralgia, fatal and non-fatal hepatic failure, hepatitis, jaundice, thrombocytopenia, depression, sleep disorders (including insomnia and nightmares), peripheral neuropathy, interstitial lung disease, and gynecomastia. Because these reactions are reported voluntarily from a population of uncertain size, it is not always possible to reliably estimate their frequency or establish a causal relationship to drug exposure.
There have been rare reports of immune-mediated necrotizing myopathy associated with statin use [see Warnings and Precautions (5.1)].
There have been rare postmarketing reports of cognitive impairment (e.g., memory loss, forgetfulness, amnesia, memory impairment, confusion) associated with statin use. These cognitive issues have been reported for all statins. The reports are generally nonserious, and reversible upon statin discontinuation, with variable times to symptom onset (1 day to years) and symptom resolution (median of 3 weeks).

7 DRUG INTERACTIONS

7.1 Cyclosporine

Cyclosporine increased rosuvastatin exposure and may result in increased risk of myopathy. Therefore, in patients taking cyclosporine, the dose of rosuvastatin calcium should not exceed 5 mg once daily [see Dosage and Administration (2.4), Warnings and Precautions (5.1), and Clinical Pharmacology (12.3)].

7.2 Gemfibrozil

Gemfibrozil significantly increased rosuvastatin exposure. Due to an observed increased risk of myopathy/rhabdomyolysis, combination therapy with rosuvastatin calcium and gemfibrozil should be avoided. If used together, the dose of rosuvastatin calcium should not exceed 10 mg once daily [ see Clinical Pharmacology (12.3) ].

7.3 Protease Inhibitors

Coadministration of rosuvastatin with certain protease inhibitors has differing effects on rosuvastatin exposure and may increase risk of myopathy. Simeprevir, which is a hepatitis C virus (HCV) protease inhibitor, or combinations of atazanavir/ritonavir or lopinavir/ritonavir, which are HIV-1 protease inhibitors, increase rosuvastatin exposure [see Table 4 –Clinical Pharmacology (12.3)].For these protease inhibitors, the dose of rosuvastatin calcium should not exceed 10 mg once daily. The combinations of fosamprenavir/ritonavir or tipranavir/ritonavir, which are HIV-1 protease inhibitors, produce little or no change in rosuvastatin exposure. Caution should be exercised when rosuvastatin is coadministered with protease inhibitors [see Dosage and Administration (2.4), Warnings and Precautions (5.1) and Clinical Pharmacology (12.3)].

7.4 Coumarin Anticoagulants

Rosuvastatin calcium significantly increased INR in patients receiving coumarin anticoagulants. Therefore, caution should be exercised when coumarin anticoagulants are given in conjunction with rosuvastatin calcium. In patients taking coumarin anticoagulants and rosuvastatin calcium concomitantly, INR should be determined before starting rosuvastatin calcium and frequently enough during early therapy to ensure that no significant alteration of INR occurs [see Warnings and Precautions (5.3) and Clinical Pharmacology (12.3)].

7.5 Niacin

The risk of skeletal muscle effects may be enhanced when rosuvastatin calcium is used in combination with lipid- modifying doses (≥1 g/day) of niacin; caution should be used when prescribing with rosuvastatin calcium [see Warnings and Precautions (5.1)].

7.6 Fenofibrate

When rosuvastatin calcium was coadministered with fenofibrate, no clinically significant increase in the AUC of rosuvastatin or fenofibrate was observed. Because it is known that the risk of myopathy during treatment with HMG-CoA reductase inhibitors is increased with concomitant use of fenofibrates, caution should be used when prescribing fenofibrates with rosuvastatin calcium [see Warnings and Precautions (5.1) and Clinical Pharmacology (12.3)].

7.7 Colchicine

Cases of myopathy, including rhabdomyolysis, have been reported with HMG-CoA reductase inhibitors, including rosuvastatin, coadministered with colchicine, and caution should be exercised when prescribing rosuvastatin calcium with colchicine [see Warnings and Precautions (5.1)].

8 USE IN SPECIFIC POPULATIONS

8.1 Pregnancy

Risk Summary
Rosuvastatin calcium is contraindicated for use in pregnant women since safety in pregnant women has not been established and there is no apparent benefit to therapy with rosuvastatin calcium during pregnancy. Because HMG-CoA reductase inhibitors decrease cholesterol synthesis and possibly the synthesis of other biologically active substances derived from cholesterol, rosuvastatin calcium may cause fetal harm when administered to pregnant women. Rosuvastatin calcium should be discontinued as soon as pregnancy is recognized [see Contraindications (4)]. Limited published data on the use of rosuvastatin are insufficient to determine a drug-associated risk of major congenital malformations or miscarriage. In animal reproduction studies, there were no adverse developmental effects with oral administration of rosuvastatin during organogenesis at systemic exposures equivalent to a maximum recommended human dose (MRHD) of 40 mg/day in rats or rabbits (based on AUC and body surface area, respectively). In rats and rabbits, decreased pup/fetal survival occurred at 12 times and equivalent, respectively, to the MRHD of 40 mg/day [see Data].
The estimated background risk of major birth defects and miscarriage for the indicated population is unknown. In the U.S. general population, the estimated background risk of major birth defects and miscarriage in clinically recognized pregnancies is 2-4% and 15-20%, respectively.
Data
Human Data
Limited published data on rosuvastatin have not shown an increased risk of major congenital malformations or miscarriage. Rare reports of congenital anomalies have been received following intrauterine exposure to other statins. In a review of approximately 100 prospectively followed pregnancies in women exposed to simvastatin or lovastatin, the incidences of congenital anomalies, spontaneous abortions, and fetal deaths/stillbirths did not exceed what would be expected in the general population. The number of cases is adequate to exclude a ≥3 to 4-fold increase in congenital anomalies over the background incidence. In 89% of the prospectively followed pregnancies, drug treatment was initiated prior to pregnancy and was discontinued at some point in the first trimester when pregnancy was identified.
Animal Data
Rosuvastatin crosses the placenta in rats and rabbits and is found in fetal tissue and amniotic fluid at 3% and 20%, respectively, of the maternal plasma concentration following a single 25 mg/kg oral gavage dose on gestation day 16 in rats. A higher fetal tissue distribution (25% maternal plasma concentration) was observed in rabbits after a single oral gavage dose of 1 mg/kg on gestation day 18.
Rosuvastatin administration did not indicate a teratogenic effect in rats at ≤25 mg/kg/day or in rabbits ≤3 mg/kg/day (doses equivalent to the MRHD of 40 mg/day based on AUC and body surface area, respectively).
In female rats given 5, 15 and 50 mg/kg/day before mating and continuing through to gestation day 7 resulted in decreased fetal body weight (female pups) and delayed ossification at 50 mg/kg/day (10 times the human exposure at the MRHD dose of 40 mg/day based on AUC).
In pregnant rats given 2, 10 and 50 mg/kg/day of rosuvastatin from gestation day 7 through lactation day 21 (weaning), decreased pup survival occurred at 50 mg/kg/day (dose equivalent to 12 times the MRHD of 40 mg/day based body surface area).
In pregnant rabbits given 0.3, 1, and 3 mg/kg/day of rosuvastatin from gestation day 6 to day 18, decreased fetal viability and maternal mortality was observed at 3 mg/kg/day (dose equivalent to the MRHD of 40 mg/day based on body surface area).

8.2 Lactation

Risk Summary
Rosuvastatin use is contraindicated during breastfeeding [see Contraindications (4)]. Limited data indicate that rosuvastatin is present in human milk. There is no available information on the effects of the drug on the breastfed infant or the effects of the drug on milk production. Because of the potential for serious adverse reactions in a breastfed infant, advise patients thatbreastfeeding is not recommended during treatment with rosuvastatin calcium.

8.3 Females and Males of Reproductive Potential

Contraception

Rosuvastatin calcium may cause fetal harm when administered to a pregnant woman [see Use in Specific Populations (8.1)]. Advise females of reproductive potential to use effective contraception during treatment with rosuvastatin calcium.

8.4 Pediatric Use

Pediatric use information for patients 7 to 17 years of age is approved for AstraZeneca’s CRESTOR (rosuvastatin calcium) tablets. However, due to AstraZeneca’s marketing exclusivity rights, this drug product is not labeled with that pediatric information.

8.5 Geriatric Use

Of the 10,275 patients in clinical studies with rosuvastatin calcium, 3159 (31%) were 65 years and older, and 698 (6.8%) were 75 years and older. No overall differences in safety or effectiveness were observed between these subjects and younger subjects, and other reported clinical experience has not identified differences in responses between the elderly and younger patients, but greater sensitivity of some older individuals cannot be ruled out.

Elderly patients are at higher risk of myopathy and rosuvastatin calcium should be prescribed with caution in the elderly [ see Warnings and Precautions (5.1) and Clinical Pharmacology (12.3) ].

8.6 Renal Impairment

Rosuvastatin exposure is not influenced by mild to moderate renal impairment (CLcr ≥ 30 mL/min/1.73 m^2). Exposure to rosuvastatin is increased to a clinically significant extent in patients with severe renal impairment (CLcr<30mL/min/1.73 m^2) who are not receiving hemodialysis and dose adjustment is required [see Dosage and Administration (2.5), Warnings and Precautions (5.1) and Clinical Pharmacology (12.3)].

8.7 Hepatic Impairment

Rosuvastatin calciumis contraindicated in patients with active liver disease, which may include unexplained persistent elevations of hepatic transaminase levels. Chronic alcohol liver disease is known to increase rosuvastatin exposure; rosuvastatin calciumshould be used with caution in these patients [see Contraindications (4), Warning and Precautions (5.2), and Clinical Pharmacology (12.3)].

8.8 Asian Patients

Pharmacokinetic studies have demonstrated an approximate 2-fold increase in median exposure to rosuvastatin in Asian subjects when compared with Caucasian controls. Rosuvastatin calcium dosage should be adjusted in Asian patients [see Dosage and Administration (2.3) and Clinical Pharmacology (12.3)].

10 OVERDOSAGE

There is no specific treatment in the event of overdose. In the event of overdose, the patient should be treated symptomatically and supportive measures instituted as required. Hemodialysis does not significantly enhance clearance of rosuvastatin.

11 DESCRIPTION

Rosuvastatin calcium, USP is a synthetic lipid-lowering agent for oral administration.
The chemical name for rosuvastatin calcium is bis [(E)-7-[4-(4-fluorophenyl)-6-isopropyl-2 [methyl (methylsulfonyl) amino] pyrimidin-5-yl] (3R,5S)-3, 5-dihydroxyhept-6-enoic acid] calcium salt with the following structural formula:

The molecular formula for rosuvastatin calcium, USP is (C22H27FN3O6S)2 Ca and the molecular weight is 1001.14. Rosuvastatin calcium is a white amorphous powder that is sparingly soluble in water and ethanol, and slightly soluble in ethanol. Rosuvastatin calcium is a hydrophilic compound with a partition coefficient (octanol/water) of 0.13 at pH of 7.0.
Rosuvastatin tablets, USP for oral administration contain 5, 10, 20, or 40 mg of rosuvastatin and the following inactive ingredients: Each tablet contains: crospovidone, hypromellose, lactose monohydrate magnesium stearate, mannitol, meglumine, microcrystalline cellulose, pregelatinized starch, titanium dioxide and triacetin. Additionally, 10 mg, 20 mg and 40 mg tablets contain FD&C red No. 40/allura red AC aluminum lake, FD&C blue No. 2/indigo carmine aluminum lake and FD&C yellow No.6/sunset yellow FCF aluminum lake.
Meets USP Dissolution Test 2.

12 CLINICAL PHARMACOLOGY

12.1 Mechanism of Action

Rosuvastatin is a selective and competitive inhibitor of HMG-CoA reductase, the rate-limiting enzyme that converts 3-hydroxy-3-methylglutaryl coenzyme A to mevalonate, a precursor of cholesterol. In vivo studies in animals and in vitro studies in cultured animal and human cells have shown rosuvastatin to have a high uptake into, and selectivity for, action in the liver, the target organ for cholesterol lowering. In in vivo and in vitro studies, rosuvastatin produces its lipid-modifying effects in two ways. First, it increases the number of hepatic LDL receptors on the cell-surface to enhance uptake and catabolism of LDL. Second, rosuvastatin inhibits hepatic synthesis of VLDL, which reduces the total number of VLDL and LDL particles.

12.2 Pharmacodynamics

Rosuvastatin dose dependently reduces elevated LDL-cholesterol and reduces total cholesterol and triglycerides and increases HDL-cholesterol [ see Clinical Studies (14)]. A therapeutic response to rosuvastatin calcium is evident within 1 week of commencing therapy and 90% of maximum response is usually achieved in 2 weeks. The maximum response is usually achieved by 4 weeks and is maintained after that. Individualization of drug dosage should be based on the therapeutic response [ see Dosage and Administration (2)].

12.3 Pharmacokinetics

Absorption
In clinical pharmacology studies in man, peak plasma concentrations of rosuvastatin were reached 3 to 5 hours following oral dosing. Both Cmax and AUC increased in approximate proportion to rosuvastatin calcium dose. The absolute bioavailability of rosuvastatin is approximately 20%.
Administration of rosuvastatin calcium with food did not affect the AUC of rosuvastatin.
The AUC of rosuvastatin does not differ following evening or morning drug administration.
Distribution
Mean volume of distribution at steady-state of rosuvastatin is approximately 134 liters.
Rosuvastatin is 88% bound to plasma proteins, mostly albumin. This binding is reversible and independent of plasma concentrations.
Elimination
Rosuvastatin is primarily eliminated by excretion in the feces. The elimination half-life of rosuvastatin is approximately 19 hours.
Metabolism
Rosuvastatin is not extensively metabolized; approximately 10% of a radiolabeled dose is recovered as metabolite. The major metabolite is N-desmethyl rosuvastatin, which is formed principally by cytochrome P450 \ 2C9, and in vitro studies have demonstrated that N-desmethyl rosuvastatin has approximately one-sixth to one-half the HMG-CoA reductase inhibitory activity of the parent compound. Overall, greater than 90% of active plasma HMG-CoA reductase inhibitory activity is accounted for by the parent compound.
Excretion
Following oral administration, rosuvastatin and its metabolites are primarily excreted in the feces (90%). After an intravenous dose, approximately 28% of total body clearance was via the renal route, and 72% by the hepatic route.
Specific Populations
Racial or Ethnic Groups
A population pharmacokinetic analysis revealed no clinically relevant differences in pharmacokinetics among Caucasian, Hispanic, and Black or Afro-Caribbean groups. However, pharmacokinetic studies, including one conducted in the US, have demonstrated an approximate 2-fold elevation in median exposure (AUC and Cmax) in Asian subjects when compared with a Caucasian control group.
Male and Female Patients
There were no differences in plasma concentrations of rosuvastatin between men and women.
Pediatric use information for patients ages 8 to less than 10 years is approved for AstraZeneca’s CRESTOR (rosuvastatin calcium) tablets. However, due to AstraZeneca’s marketing exclusivity rights, this drug product is not labeled with that pediatric information.
Geriatricpatients
There were no differences in plasma concentrations of rosuvastatin between the nonelderly and elderly populations (age ≥ 65 years).
Patients with Renal Impairment
Mild to moderate renal impairment (CLcr ≥ 30 mL/min/1.73 m^2) had no influence on plasma concentrations of rosuvastatin. However, plasma concentrations of rosuvastatin increased to a clinically significant extent (about 3-fold) in patients with severe renal impairment (CLcr < 30 mL/min/1.73 m2) not receiving hemodialysis compared with healthy subjects (CLcr > 80 mL/min/1.73 m2).
Hemodialysis
Steady-state plasma concentrations of rosuvastatin in patients on chronic hemodialysis were approximately 50% greater compared with healthy volunteer subjects with normal renal function.
Patients with Hepatic Impairment
In patients with chronic alcohol liver disease, plasma concentrations of rosuvastatin were modestly increased.
In patients with Child-Pugh A disease, Cmax and AUC were increased by 60% and 5%, respectively, as compared with patients with normal liver function. In patients with Child-Pugh B disease, Cmax and AUC were increased 100% and 21%, respectively, compared with patients with normal liver function.
Drug-Interactions Studies
Rosuvastatin clearance is not dependent on metabolism by cytochrome P450 3A4 to a clinically significant extent.
Rosuvastatin is a substrate for certain transporter proteins including the hepatic uptake transporter organic anion-transporting polyprotein 1B1 (OATP1B1) and efflux transporter breast cancer resistance protein (BCRP). Concomitant administration of rosuvastatin calcium with medications that are inhibitors of these transporter proteins (e.g. cyclosporine, certain HIV protease inhibitors) may result in increased rosuvastatin plasma concentrations [ see Dosage and Administration (2.4)] and Drug Interactions (7.1, 7.3].

Table 4. Effect of Coadministered Drugs on Rosuvastatin Systemic Exposure

Coadministered drug and dosing regimen | Rosuvastatin
 |  | Mean Ratio (ratio with/without coadministered drug) No Effect = 1.0
 | Dose (mg)^1 | Change in AUC | Change in Cmax
Cyclosporine – stable dose required (75 mg – 200 mg BID) | 10 mg QD for 10 days | 7.1 ^2 | 11 ^2
Atazanavir/ritonavir combination 300 mg/100 mg QD for 8 days | 10 mg | 3.1 ^2 | 7 ^2
Simeprevir 150 mg QD, 7 days | 10 mg, single dose | 2.8 ^2 (2.3 to 3.4) ^3 | 3.2 ^2 (2.6 to 3.9) ^3
Lopinavir/ritonavir combination 400 mg/100 mg BID for 17 days | 20 mg QD for 7 days | 2.1 ^2 (1.7 to 2.6) ^3 | 5^2 (3.4 to 6.4) ^3
Gemfibrozil 600 mg BID for 7 days | 80 mg | 1.9 ^2 (1.6 to 2.2) ^3 | 2.2^2 (1.8 to 2.7) ^3
Eltrombopag 75 mg QD, 5 days | 10 mg | 1.6 (1.4 to 1.7) ^3 | 2 (1.8 to 2.3) ^3
Darunavir 600 mg/ritonavir 100 mg BID, 7 days | 10 mg QD for 7 days | 1.5 (1.0 to 2.1) ^3 | 2.4 (1.6 to 3.6) ^3
Tipranavir/ritonavir combination 500 mg/200mg BID for 11 days | 10 mg | 1.4 (1.2 to 1.6) ^3 | 2.2 (1.8 to 2.7) ^3
Dronedarone 400 mg BID | 10 mg | 1.4
Itraconazole 200 mg QD, 5 days | 10 mg or 80 mg | 1.4 (1.2 to 1.6) ^3 1.3 (1.1 to 1.4) ^3 | 1.4 (1.2 to 1.5) ^3 1.2 (0.9 to 1.4) ^3
Ezetimibe 10 mg QD, 14 days | 10 mg QD for 14 days | 1.2 (0.9 to 1.6) ^3 | 1.2 (0.8 to 1.6) ^3
Fosamprenavir/ritonavir 700 mg/100 mg BID for 7 days | 10 mg | 1.1 | 1.5
Fenofibrate 67 mg TID for 7 days | 10 mg | ↔ | 1.2 (1.1 to 1.3) ^3
Rifampicin 450 mg QD, 7 days | 20 mg | ↔
Aluminum & magnesium hydroxide combination antacid Administered simultaneously Administered 2 hours apart | 40 mg 40 mg | 0.5 ^2 (0.4 to 0.5) ^3 0.8 (0.7 to 0.9) ^3 | 0.5 ^2 (0.4 to 0.6) ^3 0.8 (0.7 to 1.0) ^3
Ketoconazole 200 mg BID for 7 days | 80 mg | 1.0 (0.8 to 1.2) ^3 | 1.0 (0.7 to 1.3) ^3
Fluconazole 200 mg QD for 11 days | 80 mg | 1.1 (1.0 to 1.3) ^3 | 1.1 (0.9 to 1.4) ^3
Erythromycin 500 mg QID for 7 days | 80 mg | 0.8 (0.7 to 0.9) ^3 | 0.7 (0.5 to 0.9) ^3

^1 Single dose unless otherwise noted.
^2 Clinically significant [ see Dosage and Administration (2)and Warnings and Precautions (5)]
^3 Mean ratio with 90% CI (with/without coadministered drug, e.g., 1= no change, 0.7 = 30% decrease, 11=11 fold increase in exposure)
Table 5. Effect of Rosuvastatin Coadministration on Systemic Exposure to Other Drugs

Rosuvastatin Dosage Regimen | Coadministered Drug
 |  | Mean Ratio (ratio with/without coadministered drug) No Effect = 1.0
 | Name and Dose | Change in AUC | Change in Cmax
40 mg QD for 10 days | Warfarin ^1 25 mg single dose | R- Warfarin 1.0 (1.0 to 1.1) ^2 S-Warfarin 1.1 (1.0 to 1.1) ^2 | R-Warfarin 1.0 (0.9 to 1.0) ^2 S-Warfarin 1.0 (0.9to 1.1) ^2
40 mg QD for 12 days | Digoxin 0.5 mg single dose | 1.0 (0.9 to 1.2) ^2 | 1.0 (0.9 to 1.2) ^2
40 mg QD for 28 days | Oral Contraceptive (ethinyl estradiol 0.035 mg & norgestrel 0.180, 0.215 and 0.250 mg) QD for 21 Days | EE 1.3 (1.2 to 1.3) ^2 NG 1.3 (1.3 to 1.4) ^2 | EE 1.3 (1.2 to 1.3) ^2 NG 1.2 (1.1 to 1.3) ^2

EE = ethinyl estradiol, NG = norgestrel
^1Clinically significant pharmacodynamic effects [ see Warnings and Precautions (5.3)]
^2 Mean ratio with 90% CI (with/without coadministered drug, e.g., 1= no change, 0.7=30% decrease, 11=11-fold increase in exposure)

12.5 Pharmacogenomics

Disposition of HMG-CoA reductase inhibitors, including rosuvastatin, involves OATP1B1 and other transporter proteins. Higher plasma concentrations of rosuvastatin have been reported in very small groups of patients (n=3 to 5) who have two reduced function alleles of the gene that encodes OATP1B1 (SLCO1B1 521T > C). The frequency of this genotype (i.e., SLCO1B1 521 C/C) is generally lower than 5% in most racial/ethnic groups. The impact of this polymorphism on efficacy and/or safety of rosuvastatin has not been clearly established.

13 NONCLINICAL TOXICOLOGY

13.1 Carcinogenesis, Mutagenesis, Impairment of Fertility

In a 104-week carcinogenicity study in rats at dose levels of 2, 20, 60, or 80 mg/kg/day by oral gavage, the incidence of uterine stromal polyps was significantly increased in females at 80 mg/kg/day at systemic exposure 20 times the human exposure at 40 mg/day based on AUC. Increased incidence of polyps was not seen at lower doses.

In a 107-week carcinogenicity study in mice given 10, 60 or 200 mg/kg/day by oral gavage, an increased incidence of hepatocellular adenoma/carcinoma was observed at 200 mg/kg/day at systemic exposures 20 times the human exposure at 40 mg/day based on AUC. An increased incidence of hepatocellular tumors was not seen at lower doses.

Rosuvastatin was not mutagenic or clastogenic with or without metabolic activation in the Ames test with Salmonella typhimurium and Escherichia coli, the mouse lymphoma assay, and the chromosomal aberration assay in Chinese hamster lung cells. Rosuvastatin was negative in the in vivo mouse micronucleus test.

In rat fertility studies with oral gavage doses of 5, 15, 50 mg/kg/day, males were treated for 9 weeks prior to and throughout mating and females were treated 2 weeks prior to mating and throughout mating until gestation day 7. No adverse effect on fertility was observed at 50 mg/kg/day (systemic exposures up to 10 times the human exposure at 40 mg/day based on AUC). In testicles of dogs treated with rosuvastatin at 30 mg/kg/day for one month, spermatidic giant cells were seen. Spermatidic giant cells were observed in monkeys after 6-month treatment at 30 mg/kg/day in addition to vacuolation of seminiferous tubular epithelium. Exposures in the dog were 20 times and in the monkey 10 times the human exposure at 40 mg/day based on body surface area. Similar findings have been seen with other drugs in this class.

13.2 Animal Toxicology and / or Pharmacology

Central Nervous System Toxicity
CNS vascular lesions, characterized by perivascular hemorrhages, edema, and mononuclear cell infiltration of perivascular spaces, have been observed in dogs treated with several other members of this drug class. A chemically similar drug in this class produced dose-dependent optic nerve degeneration (Wallerian degeneration of retinogeniculate fibers) in dogs, at a dose that produced plasma drug levels about 30 times higher than the mean drug level in humans taking the highest recommended dose. Edema, hemorrhage, and partial necrosis in the interstitium of the choroid plexus was observed in a female dog sacrificed moribund at day 24 at 90 mg/kg/day by oral gavage (systemic exposures 100 times the human exposure at 40 mg/day based on AUC). Corneal opacity was seen in dogs treated for 52 weeks at 6 mg/kg/day by oral gavage (systemic exposures 20 times the human exposure at 40 mg/day based on AUC). Cataracts were seen in dogs treated for 12 weeks by oral gavage at 30 mg/kg/day (systemic exposures 60 times the human exposure at 40 mg/day based on AUC). Retinal dysplasia and retinal loss were seen in dogs treated for 4 weeks by oral gavage at 90 mg/kg/day (systemic exposures 100 times the human exposure at 40 mg/day based on AUC). Doses ≤30 mg/kg/day (systemic exposures ≤ 60 times the human exposure at 40 mg/day based on AUC) did not reveal retinal findings during treatment for up to one year.
Juvenile Toxicology Study
In a juvenile study, rats were dosed by oral gavage with 10 or 50 mg/kg/day from weaning for 9 weeks prior to pairing, throughout pairing and up to the day before necropsy for males or up to gestation day 7 for females. No effects on sexual development, testicular and epididymal appearance or fertility were observed at either dose level.
Pediatric information is approved for AstraZeneca’s CRESTOR (rosuvastatin calcium) tablets. However, due to AstraZeneca’s marketing exclusivity rights, this drug product is not labeled with that pediatric information.

14 CLINICAL STUDIES

14.3 Hypertriglyceridemia

Dose-Response Study: In a double-blind, placebo-controlled dose-response study in patients with baseline TG levels from 273 to 817 mg/dL, rosuvastatin calcium given as a single daily dose (5 to 40 mg) over 6 weeks significantly reduced serum TG levels (Table 9).

Table 9. Dose-Response in Patients with Primary Hypertriglyceridemia Over 6 Weeks Dosing Median (Min, Max) Percent Change From Baseline

Dose | Placebo (n=26) | Rosuvastatin calcium 5 mg (n=25) | Rosuvastatin calcium 10 mg (n=23) | Rosuvastatin calcium 20 mg (n=27) | Rosuvastatin calcium 40 mg (n=25)
Triglycerides | 1 (-40, 72) | -21 (-58, 38) | -37 (-65, 5) | -37 (-72, 11) | -43 (-80, -7)
nonHDL-C | 2 (-13, 19) | -29 (-43, -8) | -49 (-59, -20) | -43 (-74, 12) | -51 (-62, -6)
VLDL-C | 2 (-36, 53) | -25 (-62, 49) | -48 (-72, 14) | -49 (-83, 20) | -56 (-83, 10)
Total-C | 1 (-13, 17) | -24 (-40, -4) | -40 (-51, -14) | -34 (-61, -11) | -40 (-51, -4)
LDL-C | 5 (-30, 52) | -28 (-71, 2) | -45 (-59, 7) | -31 (-66, 34) | -43 (-61, -3)
HDL-C | -3 (-25, 18) | 3 (-38, 33) | 8 (-8, 24) | 22 (-5, 50) | 17 (-14, 63)

14.4 Primary Dysbetalipoproteinemia (Type III Hyperlipoproteinemia)

In a randomized, multicenter, double-blind crossover study, 32 patients (27 with є2/є2 and 4 with apo E mutation [Arg145Cys] with primary dysbetalipoproteinemia (Type III Hyperlipoproteinemia) entered a 6-week dietary lead-in period on the NCEP Therapeutic Lifestyle Change (TLC) diet. Following dietary lead-in, patients were randomized to a sequence of treatments in conjunction with the TLC diet for 6 weeks each: rosuvastatin 10 mg followed by rosuvastatin 20 mg or rosuvastatin 20 mg followed by rosuvastatin 10 mg. Rosuvastatin calcium reduced non HDL-C (primary end point) and circulating remnant lipoprotein levels. Results are shown in the table below.

Table 10. Lipid-modifying Effects of Rosuvastatin 10 mg and 20 mg in Primary Dysbetalipoproteinemia (Type III hyperlipoproteinemia) after Six weeks by Median Percent Change(95% CI) from Baseline (N=32)
 | Median at Baseline (mg/dL) | Median percent change from baseline (95% CI) Rosuvastatin calcium 10 mg | Median percent change from baseline (95% CI) Rosuvastatin calcium 20 mg
Total-C | 342.5 | – 43.3 (-46.9, – 37.5) | -47.6 (-51.6,-42.8)
Triglycerides | 503.5 | -40.1 (-44.9, -33.6) | -43.0 (-52.5, -33.1)
NonHDL-C | 294.5 | - 48.2 (-56.7, -45.6) | -56.4 (-61.4, -48.5)
VLDL-C + IDL-C | 209.5 | -46.8 (-53.7, -39.4) | -56.2 (-67.7, -43.7)
LDL-C | 112.5 | -54.4 (-59.1, -47.3) | -57.3 (-59.4, -52.1)
HDL-C | 35.5 | 10.2 (1.9, 12.3) | 11.2 (8.3, 20.5)
RLP-C | 82.0 | -56.4 (-67.1, -49.0) | -64.9 (-74.0, -56.6)
Apo-E | 16.0 | -42.9 (-46.3, -33.3) | -42.5 (-47.1, -35.6)

14.5 Homozygous Familial Hypercholesterolemia

Dose-Titration Study:In an open-label, forced-titration study, homozygous FH patients (n=40, 8-63 years)were evaluated for their response to rosuvastatin calcium 20 to 40 mg titrated at a 6-week interval. In the overall population, the mean LDL-C reduction from baseline was 22%. About one-third of the patients benefited from increasing their dose from 20 mg to 40 mg with further LDL lowering of greater than 6%. In the 27 patients with at least a 15% reduction in LDL-C, the mean LDL-C reduction was 30% (median 28% reduction). Among 13 patients with an LDL-C reduction of < 15%, 3 had no change or an increase in LDL-C. Reductions in LDL-C of 15% or greater were observed in 3 of 5 patients with known receptor negative status.

Pediatric use information for patients 7 to 17 years of age is approved for AstraZeneca’s CRESTOR (rosuvastatin calcium) tablets. However, due to AstraZeneca’s marketing exclusivity rights, this drug product is not labeled with that pediatric information.

16 HOW SUPPLIED/STORAGE AND HANDLING

Rosuvastatin Tablets,USP 20 mg are available as Pink, round shaped, biconvex, film coated tablets debossed with R20 on one side and plain on other side.

NDC 68071-2379 2 BOTTLES OF 120

Storage

Store at controlled room temperature, 20-25ºC (68-77ºF) [see USP Controlled Room Temperature]. Protect from moisture.

17 PATIENT COUNSELING INFORMATION

Advise the patient to read the FDA-approved patient labeling (Patient Information).

Patients should be instructed not to take 2 doses of rosuvastatin tablets within 12 hours of each other.
Skeletal Muscle Effects

Patients should be advised to report promptly unexplained muscle pain, tenderness, or weakness, particularly if accompanied by malaise or fever or if these muscle signs or symptoms persist after discontinuing rosuvastatin tablets.
Concomitant Use of Antacids

When taking rosuvastatin tablets with an aluminum and magnesium hydroxide combination antacid, the antacid should be taken at least 2 hours after rosuvastatin tablets administration.
Embryofetal Toxicity

Advise females of reproductive potential of the risk to a fetus, to use effective contraception during treatment, and to inform their healthcare provider of a known or suspected pregnancy. [see Contraindications (4) and Use in Specific Populations (8.1, 8.3)].
Lactation

Advise women not to breastfeed during treatment with rosuvastatin calcium [see Contraindications (4)and Use in Specific Populations (8.2)].
Liver Enzymes

It is recommended that liver enzyme tests be performed before the initiation of rosuvastatin tablets and if signs or symptoms of liver injury occur. All patients treated with rosuvastatin tablets should be advised to promptly report any symptoms that may indicate liver injury, including fatigue, anorexia, right upper abdominal discomfort, dark urine or jaundice.
Manufactured by:
MSN Laboratories Private Limited
Telangana – 509 228, INDIA
Distributed by:
Novadoz Pharmaceuticals LLc.
Piscataway, NJ 08854-3714
Issued on:
March 2019

PATIENT INFORMATION

Rosuvastatin Tablets,USP

(roe soo” va stat’ in)

Read this Patient Information carefully before you start taking rosuvastatin tablets and each time you get a refill. If you have any questions about rosuvastatin tablets, ask your doctor. Only your doctor can determine if rosuvastatin tablets are right for you.

What are Rosuvastatin tablets?

Rosuvastatin tablets are a prescription medicine that contains a cholesterol-lowering medicine called rosuvastatin calcium. Most of the cholesterol in your blood is made in the liver. Rosuvastatin tablets works by reducing cholesterol in two ways: Rosuvastatin tablets blocks an enzyme in the liver causing the liver to make less cholesterol, and Rosuvastatin tablets increases the uptake and breakdown by the liver of cholesterol already in the blood.

- Rosuvastatin tablets are used along with diet to:
  - lower the level of your “bad” cholesterol (LDL)
  - increase the level of your “good” cholesterol (HDL)
  - lower the level of fat in your blood (triglycerides)
- Rosuvastatin tablets are used to treat:
  - adults who cannot control their cholesterol levels by diet and exercise alone.

It is not known if rosuvastatin tablets are safe and effective in people who have Fredrickson Type I and V dyslipidemias.

Pediatric use information for patients 7 to 17 years of age is approved for AstraZeneca’s CRESTOR (rosuvastatin calcium) tablets. However, due to AstraZeneca’s marketing exclusivity rights, this drug product is not labeled with that pediatric information.

Who should not take rosuvastatin tablets?
Do not take rosuvastatin tablets if you:

- are allergic to rosuvastatin or any of the ingredients in rosuvastatin tablets. See the end of this leaflet for a complete list of ingredients in rosuvastatin tablets.
- have liver problems.
- are pregnant or think you may be pregnant, or are planning to become pregnant. Rosuvastatin tablets may harm your unborn baby. If you become pregnant, stop taking rosuvastatin tablets and call your doctor right away. If you are not planning to become pregnant you should use effective birth control (contraception) while you are taking rosuvastatin tablets.
- are breastfeeding. Medicines like rosuvastatin can pass into your breast milk and may harm your baby.

What should I tell my doctor before and while taking rosuvastatin tablets?
Tell your doctor if you:

- have unexplained muscle aches or weakness
- have or have had kidney problems
- have or have had liver problems
- drink more than 2 glasses of alcohol daily
- have thyroid problems
- are 65 years of age or older
- are of Asian descent
- are pregnant or think you may be pregnant, or are planning to become pregnant
- are breastfeeding

Tell your doctor about all the medicines you take, including prescription and over-the-counter medicines, vitamins, and herbal supplements.
Talk to your doctor before you start taking any new medicines.
Taking rosuvastatin tablets with certain other medicines may affect each other causing side effects. Rosuvastatin tablets may affect the way other medicines work, and other medicines may affect how rosuvastatin tablets works.

Especially tell your doctor if you take:

- cyclosporine (a medicine for your immune system)
- gemfibrozil (a fibric acid medicine for lowering cholesterol)
- anti-viral medicines including HIV or hepatitis C protease inhibitors (such as lopinavir, ritonavir, fosamprenavir, tipranavir, atazanavir, or simeprevir)
- certain anti-fungal medicines (such as itraconazole, ketoconazole and fluconazole)
- coumarin anticoagulants (medicines that prevent blood clots, such as warfarin)
- niacin or nicotinic acid
- fibric acid derivatives (such as fenofibrate)
- colchicine (a medicine used to treat gout)

Ask your doctor or pharmacist for a list of these medicines if you are not sure.
Know all of the medicines you take. Keep a list of them to show your doctor and pharmacist when you get new medicine.

How should I take rosuvastatin tablets?

- Take rosuvastatin tablets exactly as your doctor tells you to take it.
- Take rosuvastatin tablets, by mouth, 1 time each day. Swallow the tablet whole.
- Rosuvastatin tablets can be taken at any time of day, with or without food.
- Do not change your dose or stop rosuvastatin tablets without talking to your doctor, even if you are feeling well.
- Your doctor may do blood tests to check your cholesterol levels before and during your treatment with rosuvastatin tablets. Your doctor may change your dose of rosuvastatin tablets if needed.
- Your doctor may start you on a cholesterol lowering diet before giving you rosuvastatin tablets. Stay on this diet when you take rosuvastatin tablets.
- Wait at least 2 hours after taking rosuvastatin tablets to take an antacid that contains a combination of aluminum and magnesium hydroxide.
- If you miss a dose of rosuvastatin calcium tablets, take it as soon as you remember. However, do not take 2 doses of rosuvastatin tablets within 12 hours of each other.
- If you take too much rosuvastatin tablets or overdose, call your doctor or go to the nearest hospital emergency room right away.

What are the Possible Side Effects of rosuvastatin tablets?
Rosuvastatin tablets may cause serious side effects, including:

- Muscle pain, tenderness and weakness (myopathy). Muscle problems, including muscle breakdown, can be serious in some people and rarely cause kidney damage that can lead to death. Tell your doctor right away if:
  - you have unexplained muscle pain, tenderness, or weakness, especially if you have a fever or feel more tired than usual, while you take rosuvastatin tablets.
  - you have muscle problems that do not go away even after your doctor has told you to stop taking rosuvastatin tablets. Your doctor may do further tests to diagnose the cause of your muscle problems.

Your chances of getting muscle problems are higher if you:

-
  - are taking certain other medicines while you take rosuvastatin tablets
  - are 65 years of age or older
  - have thyroid problems (hypothyroidism) that are not controlled
  - have kidney problems
  - are taking higher doses of rosuvastatin tablets
- Liver problems. Your doctor should do blood tests to check your liver before you start taking rosuvastatin tablets and if you have symptoms of liver problems while you take rosuvastatin tablets. Call your doctor right away if you have any of the following symptoms of liver problems:
  - feel unusually tired or weak
  - loss of appetite
  - upper belly pain
  - dark urine
  - yellowing of your skin or the whites of your eyes

The most common side effects may include: headache, muscle aches and pains, abdominal pain, weakness, and nausea.
Additional side effects that have been reported with rosuvastatin tablets include memory loss and confusion.
Tell your doctor if you have any side effect that bothers you or that does not go away.
These are not all the possible side effects of rosuvastatin tablets. For more information, ask your doctor or pharmacist.
Call your doctor for medical advice about side effects. You may report side effects to FDA at 1-800-FDA-1088.
How should I store rosuvastatin tablets?

- Store rosuvastatin tablets at room temperature, between 68°F to 77°F (20°C to 25°C) and in a dry place.
- Safely throw away medicine that is out of date or no longer needed.

Keep rosuvastatin tablets and all medicines out of the reach of children.
What are the Ingredients in rosuvastatin tablets?

Active Ingredient: rosuvastatin as rosuvastatin calcium
Inactive Ingredients: crospovidone, hypromellose, lactose monohydrate magnesium stearate, mannitol, meglumine, microcrystalline cellulose, pregelatinized starch, titanium dioxide and triacetin. Additionally, 10 mg, 20 mg and 40 mg tablets contain FD&C red No. 40/allura red AC aluminum lake, FD&C blue No. 2/indigo carmine aluminum lake and FD&C yellow No.6/sunset yellow FCF aluminum lake.
General Information about the safe and effective use of rosuvastatin tablets
Medicines are sometimes prescribed for purposes other than those listed in a Patient Information leaflet. Do not use rosuvastatin tablets for a condition for which it was not prescribed. Do not give rosuvastatin tablets to other people, even if they have the same medical condition you have. It may harm them.
You can ask your pharmacist or doctor for information about rosuvastatin tablets that is written for health professionals.
This Patient Information has been approved by the U.S. Food and Drug Administration.
Manufactured by:
MSN Laboratories Private Limited
Telangana – 509 228,
INDIA
Distributed by:
Novadoz Pharmaceuticals LLC.
Piscataway, NJ 08854-3714
Issued on:
November 2018